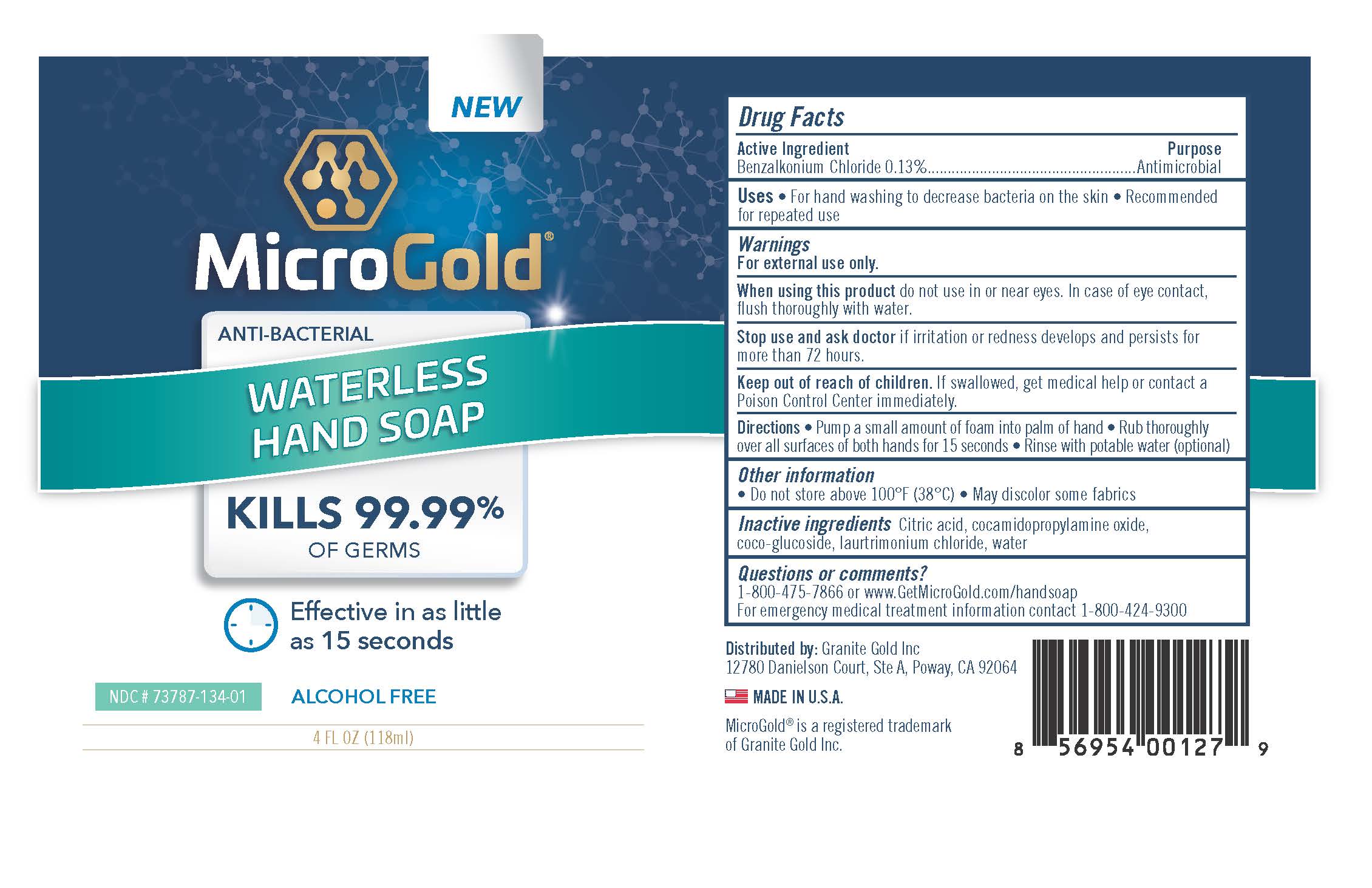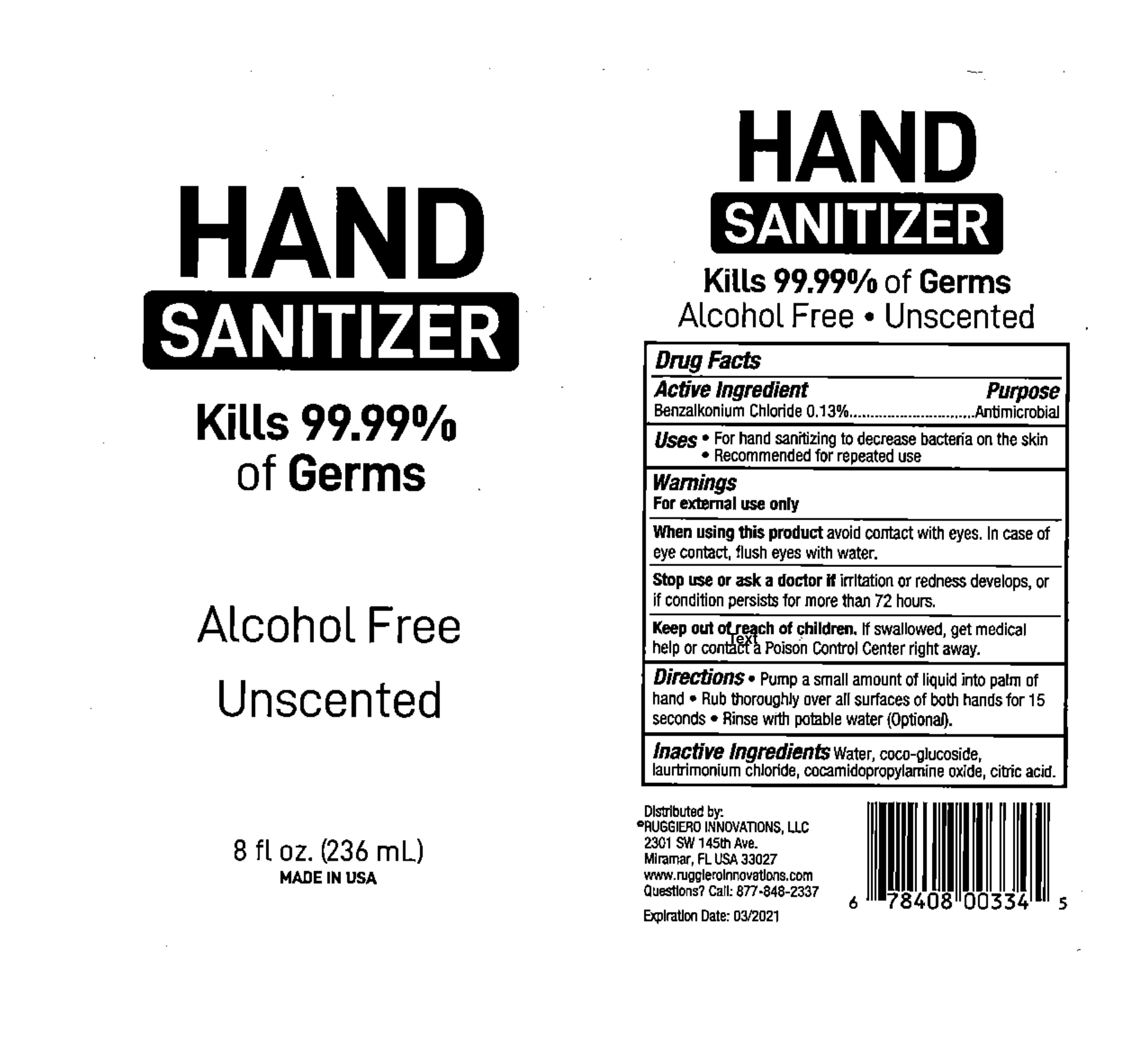 DRUG LABEL: MicroGold Anti-Bacterial Waterless Hand (4 oz.)
NDC: 73787-134 | Form: SOAP
Manufacturer: FGD, LLC
Category: otc | Type: HUMAN OTC DRUG LABEL
Date: 20210106

ACTIVE INGREDIENTS: BENZALKONIUM CHLORIDE 0.3068 g/236 mL
INACTIVE INGREDIENTS: CITRIC ACID MONOHYDRATE; WATER; COCO GLUCOSIDE; LAURTRIMONIUM CHLORIDE; COCAMIDOPROPYLAMINE OXIDE

MicroGold Anti-Bacterial Waterless hand Soap (4 oz.)

Active ingredient

Benzalkonium Chloride 0.13%

Purpose

Antimicrobial

Uses

- For hand washing to decrease bacteria on the skin
- Recommended for repeated use

Warnings

For external use only

- Do not use in or near eyes. In case of eye contact, flush thoroughly with water.

- Stop use and ask a doctor if irritation or redness develops and persists for more than 72 hours.

KEEP OUT OF REACH OF CHILDREN

If swallowed, get medical help or contact a Poison Control Center immediately.

Directions

▪ Pump a small amount of foam into palm of hand

▪ Rub thoroughly over all surfaces of both hands for 15 seconds

▪ Rinse with potable water (optional)

OTHER SAFETY INFORMATION

- Do not store above 100^0 F (38^0C)
- May Discolor some fabrics

Inactive ingredients

Citric acid, cocamidopropylamine oxide, coco-glucoside, laurtrimonium chloride, water

QUESTIONS

1-800-475-7866 or www.GetMicroGold.com/handsoap
For emergency medical treatment information contact 1-800-424-9300